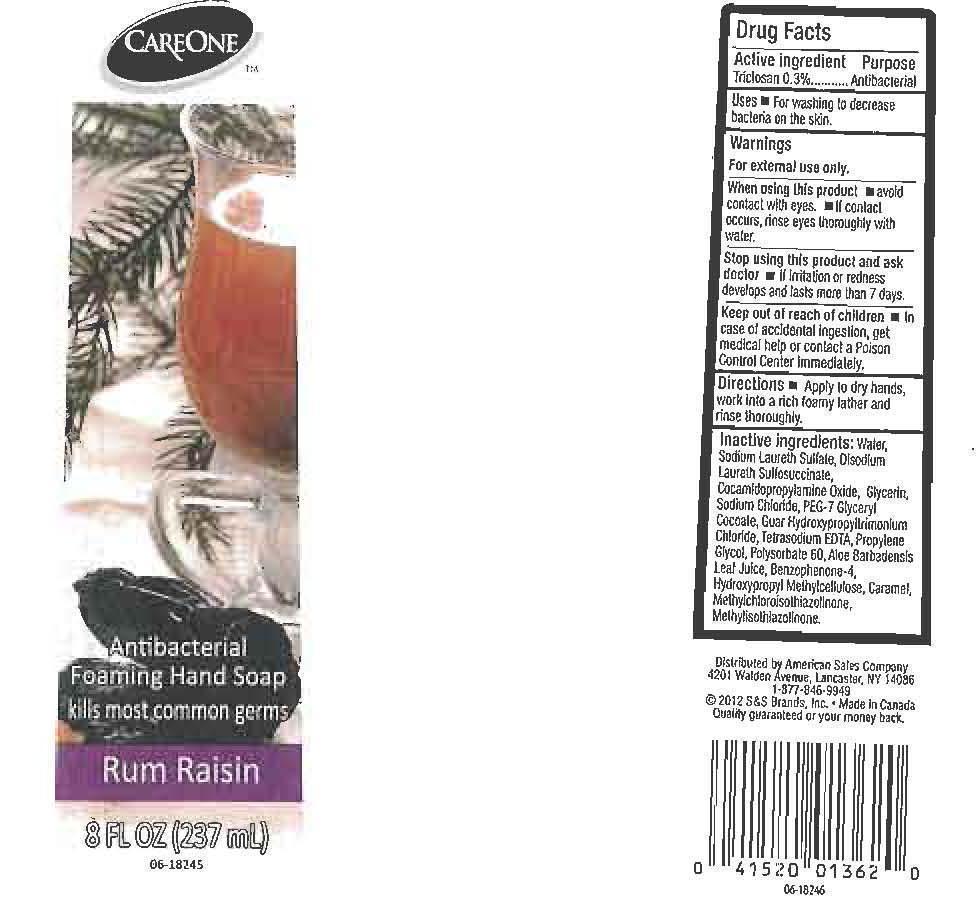 DRUG LABEL: CARE ONE
NDC: 41520-190 | Form: LIQUID
Manufacturer: AMERICAN SALES COMPANY
Category: otc | Type: HUMAN OTC DRUG LABEL
Date: 20120927

ACTIVE INGREDIENTS: TRICLOSAN 3 mg/1 mL
INACTIVE INGREDIENTS: WATER; SODIUM LAURETH SULFATE; DISODIUM LAURETH SULFOSUCCINATE; COCAMIDOPROPYLAMINE OXIDE; GLYCERIN; SODIUM CHLORIDE; PEG-7 GLYCERYL COCOATE; GUAR HYDROXYPROPYLTRIMONIUM CHLORIDE (1.7 SUBSTITUENTS PER SACCHARIDE); EDETATE SODIUM; PROPYLENE GLYCOL; POLYSORBATE 60; ALOE VERA LEAF; SULISOBENZONE; HYPROMELLOSES; CARAMEL; METHYLCHLOROISOTHIAZOLINONE; METHYLISOTHIAZOLINONE

DRUG FACTS

ACTIVE INGREDIENT

TRICLOSAN 0.3%

PURPOSE

ANTIBACTERIAL

USES

FOR WASHING TO DECREASE BACTERIA ON THE SKIN.

WARNINGS

FOR EXTERNAL USE ONLY.

WHEN USING THIS PRODUCT

AVOID CONTACT WITH EYES. IF CONTACT OCCURS, RINSE EYES THOROUGHLY WITH WATER.

STOP USING THIS PRODUCT AND ASK DOCTOR

KEEP OUT OF REACH OF CHILDREN

IN CASE OF ACCIDENTAL INGESTION, GET MEDICAL HELP OR CONTACT A POISON CONTROL CENTER IMMEDIATELY.

DIRECTIONS

APPLY TO DRY HANDS, WORK INTO A RICH FOAMY LATHER AND RINSE THOROUGHLY.

INACTIVE INGREDIENTS:

WATER (AQUA), SODIUM LAURETH SULFATE, DISODIUM LAURETH SULFOSUCCINATE, COCAMIDOPROPYLAMINE OXIDE, GLYCERIN, SODIUM CHLORIDE, PEG-7 GLYCERYL COCOATE, GUAR HYDROXYPROPYLTRIMONIUM CHLORIDE, TETRASODIUM EDTA, PROPYLENE GLYCOL, POLYSORBATE 60, ALOE BARBADENSIS LEAF JUICE, BENZOPHENONE-4, HYDROXYPROPYL METHYLCELLULOSE, CARAMEL, METHYLCHLOROISOTHIAZOLINONE, METHYLISOTHIAZOLINONE.